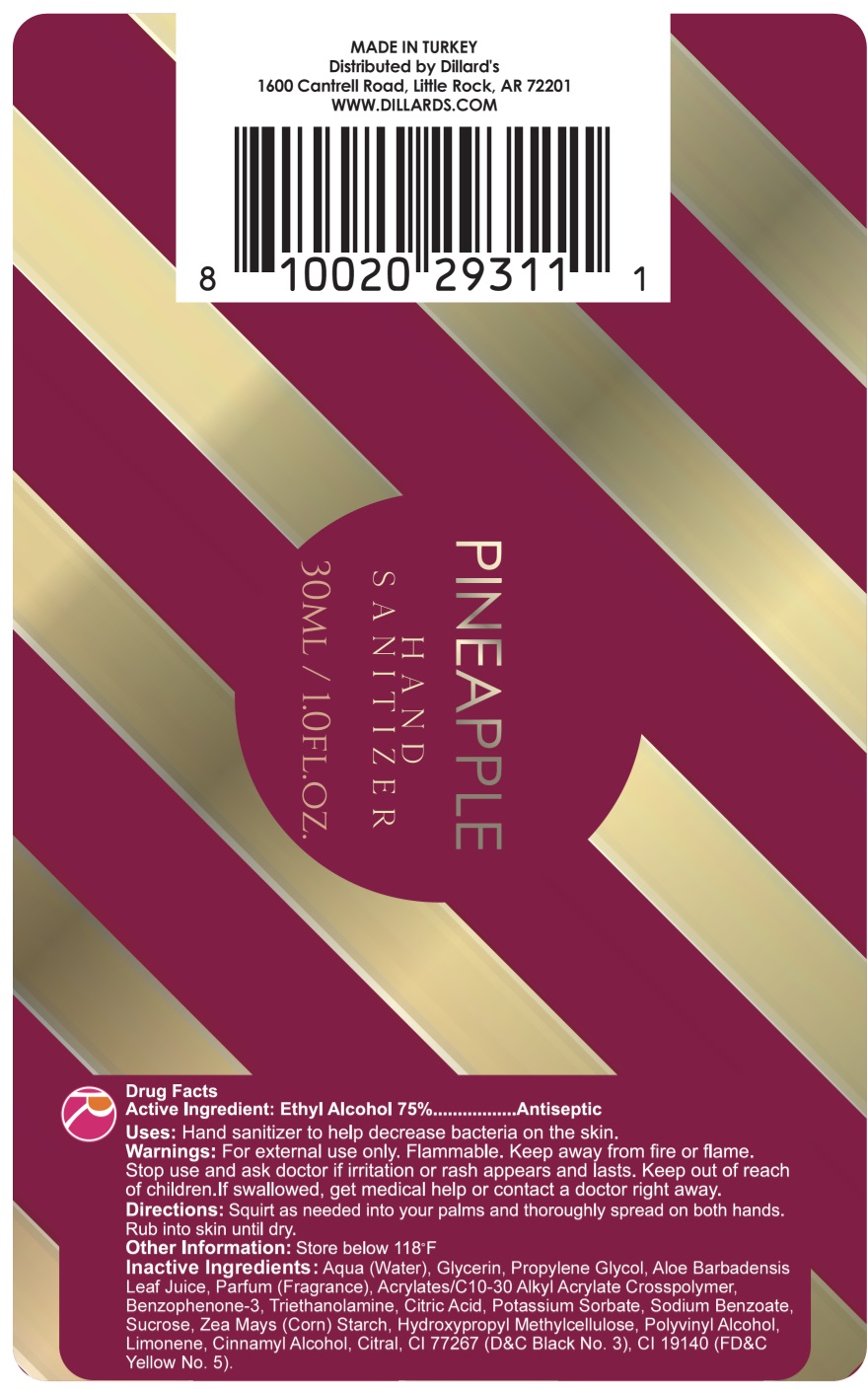 DRUG LABEL: Pineapple Hand Sanitizer 75 Ethyl Alcohol
NDC: 80026-015 | Form: GEL
Manufacturer: Reaction Retail, LLC
Category: otc | Type: HUMAN OTC DRUG LABEL
Date: 20201023

ACTIVE INGREDIENTS: ALCOHOL 0.75 mL/1 mL
INACTIVE INGREDIENTS: WATER; GLYCERIN; PROPYLENE GLYCOL; ALOE VERA LEAF; CARBOMER INTERPOLYMER TYPE A (ALLYL SUCROSE CROSSLINKED); OXYBENZONE; TROLAMINE; CITRIC ACID MONOHYDRATE; POTASSIUM SORBATE; SODIUM BENZOATE; SUCROSE; STARCH, CORN; HYPROMELLOSE, UNSPECIFIED; POLYVINYL ALCOHOL, UNSPECIFIED; LIMONENE, (+)-; CINNAMYL ALCOHOL; CITRAL; D&C BLACK NO. 2; FD&C YELLOW NO. 5

Pineapple Hand Sanitizer, 75% Ethyl Alcohol

Active Ingredient:

Ethyl Alcohol 75%

PURPOSE

Antiseptic

Uses:

Hand sanitizer to help decrease bacteria on the skin.

Warnings:

For external use only. Flammable. Keep away from fire or flame.

Stop use and ask doctor

if irritation or rash appears and lasts.

Keep out of reach of children.

If swallowed, get medical help or contact a doctor right away.

Directions:

Squirt as needed into your palms and thoroughly spread on both hands. Rub into skin until dry.

Other Information:

Store below 118°F

Inactive Ingredients:

Aqua (Water), Glycerin, Propylene Glycol, Aloe Barbadensis Leaf Juice, Parfum (Fragrance), Acrylates/C10-30 Alkyl Acrylate Crosspolymer, Benzophenone-3, Triethanolamine, Citric Acid, Potassium Sorbate, Sodium Benzoate, Sucrose, Zea Mays (Corn) Starch, Hydroxypropyl Methylcellulose, Polyvinyl Alcohol, Limonene, Cinnamyl Alcohol, Citral, CI 77267 (D&C Black No. 3), CI 19140 (FD&C Yellow No. 5).